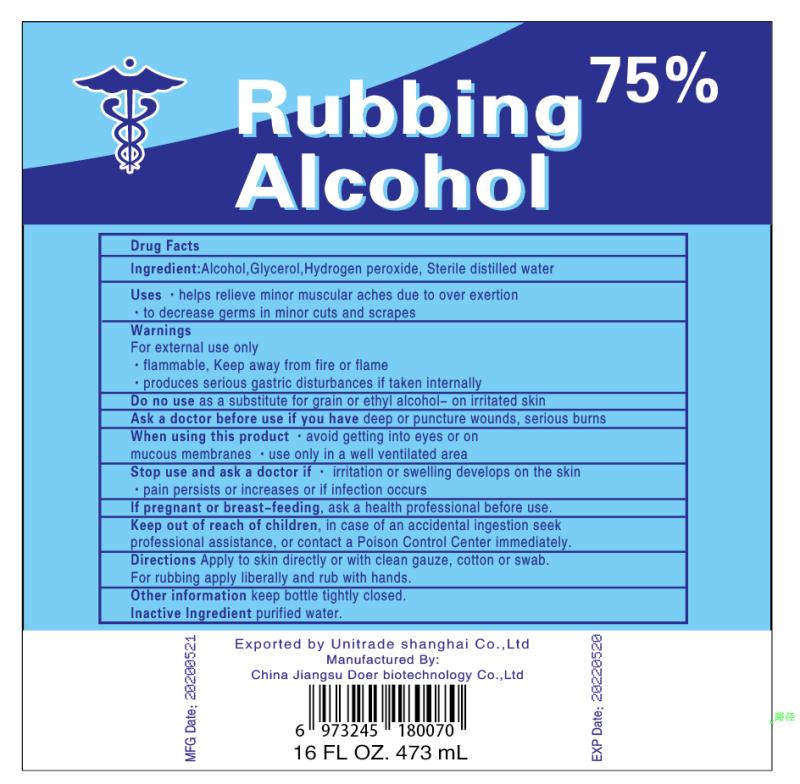 DRUG LABEL: DISINFECTANT ALCOHOL
NDC: 55449-003 | Form: LIQUID
Manufacturer: Jiangsu Doer biotechnology Co., Ltd
Category: otc | Type: HUMAN OTC DRUG LABEL
Date: 20201103

ACTIVE INGREDIENTS: ALCOHOL 354.75 mL/473 mL
INACTIVE INGREDIENTS: WATER; GLYCERIN; HYDROGEN PEROXIDE

55449-003 outcome

DOSAGE AND ADMINISTRATION

This is flammable product and required to be far away of any fire source.

INACTIVE INGREDIENT

WATER

HYDROGEN PEROXIDE

GLYCEROL

INDICATIONS AND USAGE

Apply to skin directly or with clean gauze, cotton or swab.For rubbing apply liberally and rub with hands.

ACTIVE INGREDIENT

alcohol

keep out of reach of children

PURPOSE

Disinfection
Sterilization
No Rinseing

WARNINGS

For external use only.flammable, Keep away from fire or flame,produces serious gastric disturbances if taken interally